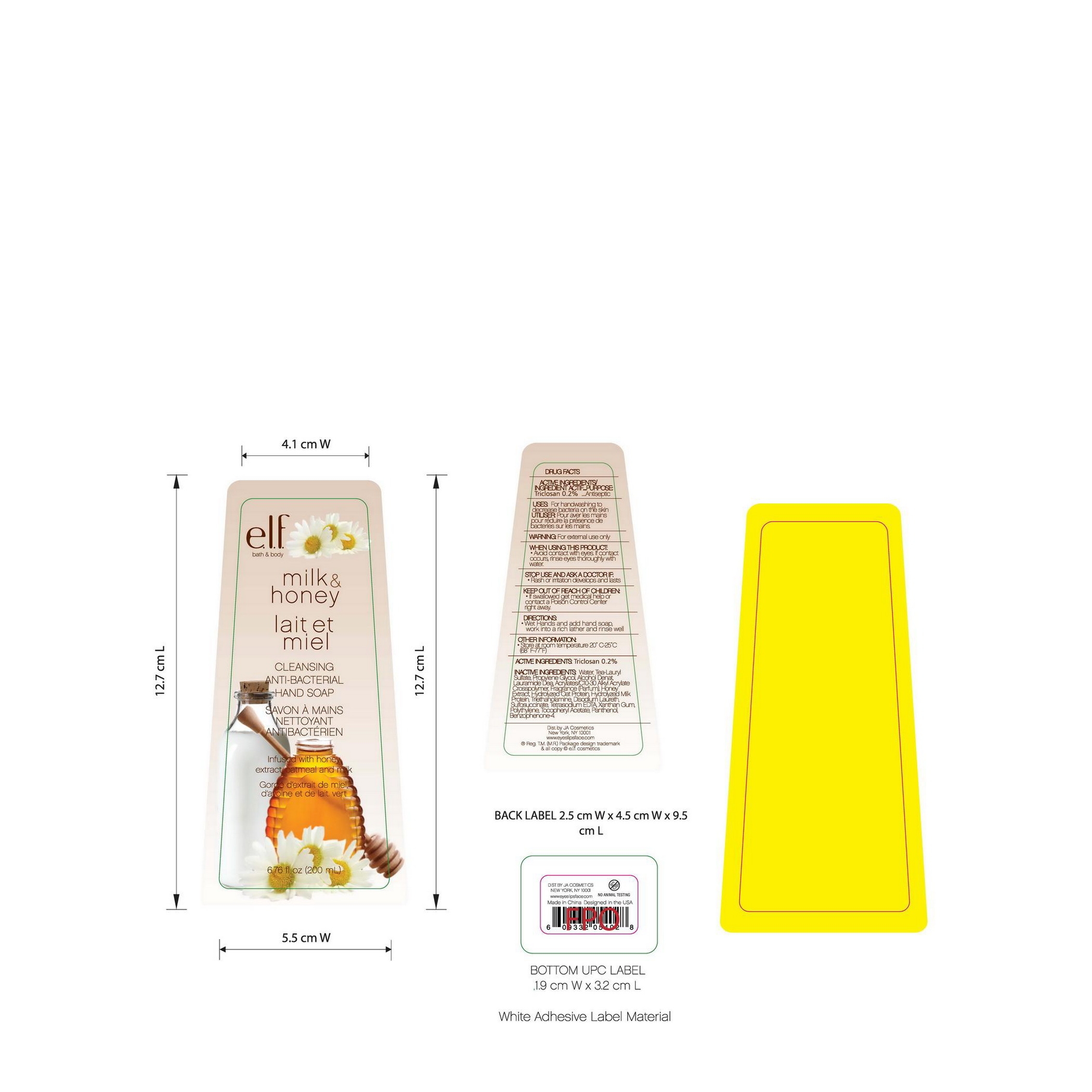 DRUG LABEL: ELF Milk and Honey Cleansing Anti-bacterial Hand
NDC: 52664-002 | Form: LIQUID
Manufacturer: Hangzhou Facecare Cosmetics Co., Ltd.
Category: otc | Type: HUMAN OTC DRUG LABEL
Date: 20101117

ACTIVE INGREDIENTS: TRICLOSAN 0.2 g/100 g
INACTIVE INGREDIENTS: WATER 73.69 g/100 g; TROLAMINE LAURYL SULFATE; PROPYLENE GLYCOL; ALCOHOL; LAURIC DIETHANOLAMIDE; CARBOMER INTERPOLYMER TYPE A (55000 CPS); HONEY; TROLAMINE; DISODIUM LAURETH SULFOSUCCINATE; EDETATE SODIUM; XANTHAN GUM; .ALPHA.-TOCOPHEROL ACETATE, DL-; PANTHENOL; SULISOBENZONE

Drug Fact

Active Ingredient:

Triclosan: 0.2%

Purpose:

Antiseptic

Use:
Cleanse skin

Warning:

For external use only

When Using This Product:

Avoid contact with eyes. If contact occurs rinse thoroughly with water

Stop Use And Ask A Doctor If:

Rash or irritation develops and lasts

Keep Out of Reach of Children:

If swallowed get medical help or contact a Poison Control Center immediately

Directions:

Wet hand and add hand soap. Work into a rich layer and rinse well.

STORAGE AND HANDLING

Other Imformation:

Store at room temperature 20-25C (68-77F)

Inactive Ingredient:

Water, Tea-Lauryl Sulfate, Propylene Glycol, Alcohol Denat, Lauramide DEA, Acrylate/C10-30 Alkyl Acrylate Crossppolymer, Fragrance,. Honey Extract, Hydrolyzed Oat Protein, Hydrolyzed Milk Protein, Triethanolamine, Disodium Laureth Sulfosuccinate, Tetrasodium EDTA, Xanthan Gum, Polyethylene, Tocopheryl Acetate, Panthenol, Benzophenone-4

PACKAGE LABEL

labe